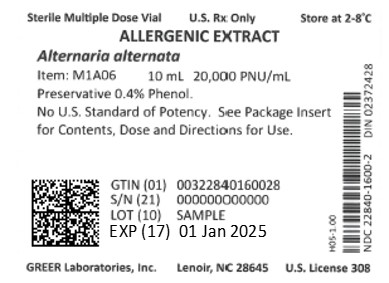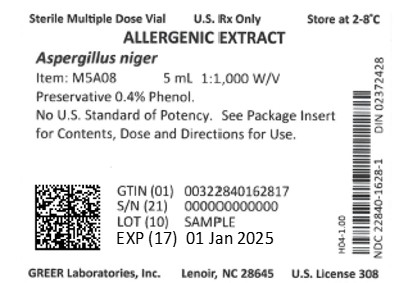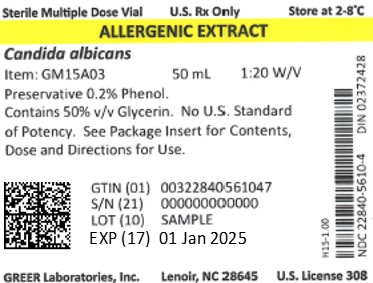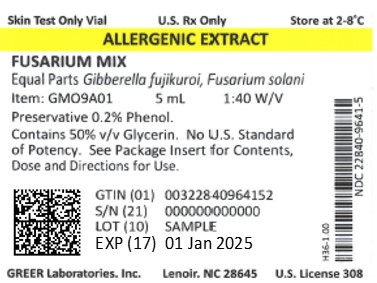 DRUG LABEL: Aspergillus Mix
NDC: 22840-9633 | Form: SOLUTION
Manufacturer: Greer Laboratories, Inc.
Category: other | Type: NON-STANDARDIZED ALLERGENIC LABEL
Date: 20250603

ACTIVE INGREDIENTS: ASPERGILLUS NIGER VAR. NIGER 0.01 g/1 mL; ASPERGILLUS FUMIGATUS 0.01 g/1 mL; EUROTIUM AMSTELODAMI 0.01 g/1 mL; ASPERGILLUS FLAVUS 0.01 g/1 mL; ASPERGILLUS NIDULANS 0.01 g/1 mL
INACTIVE INGREDIENTS: GLYCERIN; SODIUM BICARBONATE; PHENOL; SODIUM CHLORIDE

Non Standardized Allergenic Extracts
Pollens, Molds, Epidermals, Insects, Dusts, Foods, and Miscellaneous Inhalants

WARNING

THIS ALLERGENIC PRODUCT IS INTENDED FOR USE BY PHYSICIANS WHO ARE EXPERIENCED IN THE ADMINISTRATION OF ALLERGENIC EXTRACTS AND THE EMERGENCY CARE OF ANAPHYLAXIS, OR FOR USE UNDER THE GUIDANCE OF AN ALLERGY SPECIALIST.

ALLERGENIC EXTRACTS MAY CAUSE SEVERE OR FATAL ANAPHYLAXIS IN EXTREMELY SENSITIVE PATIENTS. THE INITIAL DOSE MUST BE BASED ON SKIN TESTING AS DESCRIBED IN THE DOSAGE AND ADMINISTRATION SECTION OF THIS INSERT. PATIENTS SHOULD BE INSTRUCTED TO RECOGNIZE ADVERSE REACTION SYMPTOMS AND CAUTIONED TO CONTACT THE PHYSICIAN'S OFFICE IF REACTION SYMPTOMS OCCUR. IN CERTAIN INDIVIDUALS, THESE REACTIONS COULD BE FATAL. PATIENTS SHOULD BE OBSERVED FOR AT LEAST 20 MINUTES FOLLOWING TREATMENT.

EMERGENCY MEASURES, AS WELL AS PERSONNEL TRAINED IN THEIR USE, SHOULD BE IMMEDIATELY AVAILABLE IN THE EVENT OF A LIFE‑ THREATENING REACTION. PATIENTS BEING SWITCHED FROM ONE LOT OF EXTRACT TO ANOTHER FROM THE SAME MANUFACTURER SHOULD HAVE THEIR DOSE REDUCED BY 75%.

THIS PRODUCT SHOULD NOT BE INJECTED INTRAVENOUSLY.

REFER ALSO TO THE WARNINGS, PRECAUTIONS, ADVERSE REACTIONS AND OVERDOSAGE SECTION BELOW.

DESCRIPTION

Allergenic Extracts are supplied as a sterile solution for intracutaneous or subcutaneous administration. Concentrates contain the soluble extractants of the source material with 0.5% sodium chloride and 0.54% sodium bicarbonate at a pH of 6.8 to 8.4 as aqueous extracts in water for injection or in 50% glycerin. Aqueous extracts contain 0.4% phenol as a preservative and 50% glycerinated extracts contain 0.2% phenol. Diluted aqueous extracts contain Buffered Saline with 0.5% sodium chloride, 0.04% potassium phosphate, 0.11% sodium phosphate heptahydrate, and 0.4% phenol in water for injection.

Source materials for these extracts are as follows: Pollens are collected from the respective grasses, weeds, trees, shrubs, cultured plants and flowers. Mold extracts are produced from pure culture mycelial mats. Rusts and smuts are obtained from natural growths. Epidermal extracts are produced from the hide, hair, or feathers containing the natural dander, or from separated dander. Insects are the whole body insects. House dust is made from various dusts ordinarily found in the home with the extract dialyzed to remove low‑molecular weight irritants and concentrated to an extraction ratio of 1:1. Food extracts are prepared from the edible portions of the respective foods, obtained fresh if possible. Certain diagnostic food extracts contain 0.1% sodium formaldehyde sulfoxylate as an antioxidant. Other miscellaneous inhalants involved in respiratory allergy are obtained in the naturally occurring form to which a patient may be exposed.

Extracts are labeled either by weight‑to‑volume (w/v) based on the weight of the source material to the volume of the extracting fluid, or in protein nitrogen units (PNU) based on assay with one PNU representing 0.00001 mg of protein nitrogen.

CLINICAL PHARMACOLOGY

The allergic reaction is dependent upon the presence of antigen‑specific immunoglobulin E (IgE) antibodies that are bound to specific receptors on mast cells and basophils. The presence of IgE antibodies on mast cells and basophils sensitizes these cells and, upon interaction with the appropriate allergen, histamine and other mediators are released. IgE antibody has been shown to correlate with atopic diseases such as allergic rhinitis and allergic asthma.(1‑4) In the skin these mediators are responsible for the characteristic wheal and flare (erythema) reactions upon Allergenic Extract skin testing in persons with the specific allergies.(3‑7)

Specific immunotherapy with Allergenic Extracts as employed for over 45 years is helpful in reducing symptoms associated with exposure to the offending allergens. A summary of effectiveness by the Panel on Review of Allergenic Extracts, an advisory committee to the U.S. Food and Drug Administration, has been published.(8) Several mechanisms have been proposed to explain the effectiveness of immunotherapy: an increase in antigen‑specific IgG antibodies is frequently associated with clinical effectiveness, although correlation is not consistent in all studies; there is a decrease in specific IgE; and IgE production is suppressed during periods of seasonal or high exposure to the antigen.(9) Other changes following immunotherapy have been noted including development of auto‑anti‑idiotypic antibodies; a decrease in blood basophil sensitivity to allergen; a decrease in lymphokine production and lymphocyte proliferation by cells exposed to allergen; and development of allergen‑specific suppressor cells.(10) The complete mechanisms of immunotherapy are not known and remain the subject of investigation.

INDICATIONS AND USAGE

Allergenic Extracts are indicated for the diagnosis and treatment of patients with immediate hypersensitivity allergy to the respective allergens, inhaled, ingested or otherwise introduced into contact with sensitive tissues. The diagnosis of IgE‑mediated allergy may be established by the allergy history, clinical evaluation, and skin test reactivity.(4,7,11) Immunotherapy with Allergenic Extracts is indicated when testing and patient history have identified the offending allergens and when it is not possible or practical to avoid these allergens.(12‑14) Food extracts have not been proven effective in immunotherapy.

The use of Allergenic Extracts for the above purposes should be made only by physicians with special familiarity and knowledge of allergy. (See DOSAGE AND ADMINISTRATION)

CONTRAINDICATIONS

There are no known absolute contraindications to the use of Allergenic Extracts for immunotherapy. Immunotherapy with specific antigens should not be done in those individuals who do not exhibit skin test or clinical sensitivity to the particular antigens. (See below under WARNINGS and PRECAUTIONS)

Allergenic extract injections should not be administered in the presence of diseases characterized by a bleeding diathesis.

Children with nephrotic syndrome require careful consideration and probably should not receive injection therapy because a variety of seemingly unrelated events, such as immunization, can cause an exacerbation of their nephrotic disease.

General contraindications include:

EXTREME SENSITIVITY TO THE SPECIFIC ALLERGEN ‑ Determined from previous anaphylaxis following exposure.

AUTOIMMUNE DISEASE ‑ Individuals with autoimmune disease may be at risk, due to the possibility of routine immunizations exacerbating symptoms of the underlying disease.

WARNINGS

Concentrated extracts must be diluted with a sterile diluent prior to first use on a patient for treatment or intradermal testing. Allergenic Extracts are manufactured to assure high potency and have the ability during skin testing and immunotherapy to cause serious local and systemic reactions including death in sensitive patients. Most reactions occur within 20 minutes after injection,(15) but may occur later.(16) To minimize the potential for local or systemic reactions, the relative sensitivity of the patient must be assessed from the allergic history and from clinical observations. Patients should be informed of these risks prior to skin testing and immunotherapy (see PRECAUTIONS and ADVERSE REACTIONS below).

Allergenic Extract immunotherapy doses should be lowered or temporarily withheld from patients if any of the following conditions exist:

(1) severe symptoms of rhinitis and/or asthma

(2) infection or flu accompanied by fever

(3) exposure to excessive amounts of clinically relevant allergen prior to a scheduled injection

(4) evidence of a local or systemic reaction to the preceding extract injection during a course of immunotherapy

The dosage must be reduced when modifying dosages or components in a mixture or an individual prescription, or when starting a patient on fresh extract, even though the labeled strength of the old and new vials may be the same. This reduction in dosage may be necessary due to the older vial losing potency during storage, or due to different sensitivities to different components. The amount of new extract given should not exceed 25% of the last dose given from the old vial, assuming both extracts contain comparable amounts of allergen. Any evidence of a local or generalized reaction requires a reduction in dosage during the initial stages of immunotherapy, as well as during maintenance therapy.

PRECAUTIONS

GENERAL:

Not for intravenous use!

Systemic allergic reactions may occur as a result of immunotherapy. The risk can be minimized by adherence to a careful injection schedule, which starts with a low concentration of extract and is increased slowly. Because of the danger of serious reactions, caution is needed in testing exquisitely sensitive patients, particularly with potent allergens, e.g., peanut, cottonseed, and flaxseed.(8) Such extracts should be appropriately diluted before use.

The physician must be prepared to treat anaphylaxis should it occur and have the necessary drugs and equipment on hand to do so.(17‑18) Extracts should not be administered by the patient or other individuals who are not prepared to treat anaphylaxis should it occur.

Patients receiving Allergenic Extracts should be kept under observation a minimum of twenty(20) minutes so that any adverse reaction can be observed and properly handled.(15) This time should be extended for high‑risk patients such as those with unstable asthma or those suffering an exacerbation of their symptoms.

Patients receiving beta blockers may not be responsive to beta adrenergic drugs used to treat anaphylaxis. The risks of anaphylaxis in these patients should be carefully weighed against the benefits of immunotherapy.

Check the lot number and dosage schedule of the patient to verify correctness of a prescription number, a vial number, or strength. Only after this verification has been made should an injection be given.

A separate sterile needle and syringe should be used for each patient to prevent transmission of hepatitis or other infectious agents.

INFORMATION FOR PATIENTS:

Most serious reactions following the administration of Allergenic Extracts occur within 20 minutes; the patient should remain under observation for this period of time or longer if instructed by the physician. The size of any local reaction should be recorded, because increasingly large local reactions may precede a subsequent systemic reaction with increasing dosage. The patient should be instructed to report any unusual reactions. In particular, this includes unusual swelling and/or tenderness at the injection site, or reactions such as rhinorrhea, sneezing, coughing, wheezing, shortness of breath, nausea, dizziness, or faintness. Reactions may occur some time after leaving the physician's office, in which case medical attention should be sought immediately.

DRUG INTERACTIONS: Skin test diagnosis with Allergenic Extracts is contraindicated within 24 hours after the last dose of most antihistamines, within 48 hours after the last dose of terfenadine, and within 3 weeks or longer after the last dose of astemizole. These products suppress histamine skin test reactions and could mask a positive response.

CARCINOGENESIS, MUTAGENESIS, IMPAIRMENT OF FERTILITY: There is no evidence of carcinogenicity, mutagenesis or impairment of fertility in humans from Allergenic Extracts. No long‑term studies in animals have been performed to evaluate carcinogenic potential.

PREGNANCY: PREGNANCY CATEGORY C ‑ Animal reproduction studies have not been conducted with Allergenic Extracts. It is also not known whether Allergenic Extracts can cause fetal harm when administered to a pregnant woman or whether they can affect reproduction capacity. Allergenic Extracts should be given to a pregnant woman only if clearly needed.

There is no evidence of adverse effects of Allergenic Extracts on the fetus.(8) Studies have not been performed in animals to determine whether extracts affect fertility in males or females, have teratogenic potential, or have other adverse effects on the fetus. Caution should be exercised in testing or treating pregnant females because a systemic reaction may cause an abortion as a result of uterine muscle contractions.

LABOR AND DELIVERY: There is no known information of adverse effects during labor and delivery.

NURSING MOTHERS: It is not known whether this product is excreted in human milk. Because many drugs are excreted in human milk, caution should be exercised when extracts are administered to a nursing woman.

PEDIATRIC AND GERIATRIC USE: Although most extracts have not been studied systematically in children, children and geriatric patients appear to tolerate injections of Allergenic Extracts well. Studies with pollenosis and asthma have been conducted in children (e.g. refs. 19‑21). Extract usage in children should follow the same precautions as in adults.

ADVERSE REACTIONS

Adverse systemic reactions may occur within minutes upon use of an Allergenic Extract to which a person has specific sensitivity. These reactions consist primarily of allergic symptoms such as generalized skin erythema, urticaria, pruritus, angioedema, rhinitis, wheezing, laryngeal edema, and hypotension. Less commonly, nausea, emesis, abdominal cramps, diarrhea and uterine contractions may occur. Severe reactions may cause shock and loss of consciousness. Fatalities have occurred rarely.(8,22,23) These systemic reactions occur with varying frequency in different clinics and are usually less than 1%. To some extent, the reaction rate is related to the type and dose of administered extract and to the sensitivity of the patient. In general, immunotherapy with Allergenic Extracts is considered to be safe.(24) Despite all precautions, occasional reactions are unavoidable.

Adverse systemic reactions should be treated as follows:

A. A tourniquet should be immediately applied to the extremity above the site of injection. Release the tourniquet every few minutes for a few seconds.

B. Epinephrine 1:1000 should be injected immediately in the opposite arm in amounts of 0.3 to 0.5 mL and 0.2 mL epinephrine should be administered at the site of injection. For children below the age of 6 years, adjust the dosage of epinephrine to 0.005 mL per pound of body weight per dose. Repeat epinephrine dosage in 15 minutes if necessary and if symptoms persist.

C. Adverse reactions not responding to epinephrine therapy may require the use of parenteral bronchodilators, vasopressors, oxygen, or volume replacement therapy.

Local reactions consisting of erythema, itching, swelling, tenderness and sometimes pain may occur at the injection site. These reactions may appear within a few minutes to hours and persist for several days. Local cold applications and oral antihistamines may be effective treatment. For marked and prolonged local reactions, steroids may be helpful.

OVERDOSAGE

Systemic reactions are uncommon after injection, but if the patient receives more extract than can be tolerated at that particular time and begins to experience immediate hypersensitivity anaphylaxis, the procedures listed under ADVERSE REACTIONS should be instituted.

Overdosage may occur because of an error in the volume of extract injected, or an incorrect dilution injected, or because the patient may be exposed to airborne or environmental antigens simultaneously with injection of the same antigens. In the event of a systemic reaction occurring, the dosage schedule should be carefully adjusted as outlined above under WARNINGS.

DOSAGE AND ADMINISTRATION

1. DIAGNOSTIC TESTING

For the patient with a suspected diagnosis of allergy to more than one antigen, initial skin testing should include the individual extracts. If a screening skin test with a mixture is used, a positive response should be followed by testing with the individual extracts to determine the degree of sensitivity to each and to guide in the selection of extracts and their concentration for immunotherapy if indicated. However, because a negative skin test with a mixture may not be indicative of the absence of allergy to one or more of the components due to their dilution, testing with individual extracts is more precise. False negative responses may occur if serum levels of antihistamines remain from prior medication administration (see CONTRAINDICATIONS). The use of a positive control is especially recommended for patients on prior medications which may decrease the histamine skin test response.

Scratch or Prick‑puncture Skin Testing:

Allergenic Extract concentrates may be used for scratch or prick‑puncture testing or scratch tests in 50% glycerin, 1:20 w/v or strongest available strength in 5 mL vials may be used. Prick‑puncture tests with concentrated extracts in patients highly sensitive to the specific antigen should yield distinctive wheals with diameters of greater than 5 mm and with much larger erythema reactions. Glycerinated histamine phosphate 5 mg/mL (1.8 mg/mL histamine base) or aqueous histamine phosphate 2.75 mg/mL (1 mg/mL histamine base; 1:1,000 W/V) may be used as a positive control.

Intradermal Skin Testing:

Extract for intradermal testing must be prepared by diluting the stock concentrate injection vials with sterile diluent (use normal or buffered saline, or normal saline with human serum albumin) or the appropriate dilutions may be purchased.

a. Patients with a negative scratch or prick‑puncture test:

Patients who do not react to a scratch or prick‑puncture test should be tested intradermally, using a 26 or 27 gauge 1/4 inch needle, with 0.02 to 0.05 mL of an appropriate extract dilution from 1/100 to 1/1000 of the concentrate. A negative test should be followed by a repeat test using a higher concentration until significant wheal and flare reaction sizes are attained or until the responses remain negative. As a negative control use the diluent or, in the case of extracts in 50% glycerin, use 0.5% to 1% glycerosaline solution. As a positive control, use glycerinated histamine phosphate diluted to 0.5 mg/mL (0.18 mg/mL histamine base) or aqueous histamine phosphate 0.275 mg/mL (0.1 mg/mL histamine base).

b. Patients tested only by the intradermal method:

Since highly reactive individuals may react intracutaneously at 1:1 million or even 1:10 million dilutions, any intradermal injection should be preceded by a puncture test and the dose adjusted accordingly. Other patients suspected of being moderately allergic should be tested with 0.02 to 0.05 mL of an appropriate extract dilution on the order of 1/10,000 to 1/100,000 of the concentrate. A negative test should be followed by repeat tests using progressively stronger ten‑fold concentrations until significant wheal and flare reaction sizes are attained, or until skin test responses with the higher concentrations remain negative. As a negative control, use the diluent or, in the case of extracts in 50% glycerin, use 0.5% to 1% glycerosaline solution. As a positive control, use glycerinated histamine phosphate diluted to 0.5 mg/mL (0.18 mg/mL histamine base) or aqueous histamine phosphate 0.275 mg/mL (0.1 mg/mL histamine base).

Skin tests are graded in terms of the wheal and erythema response noted at 15 to 20 minutes, and compared to the appropriate controls. Wheal and erythema sizes may be recorded by actual measurement.

2. IMMUNOTHERAPY

Immunotherapy is administered by subcutaneous injection. Dosage of Allergenic Extracts is individualized according to the patient's sensitivity, the clinical response, and tolerance to the extract administered during the phases of an injection regimen. The initial dose of the extract should be determined based on the puncture test reactivity. In patients who appear to be exquisitely sensitive by history and skin test, the initial dose of the extract should be 0.05 to 0.1 mL of a low concentration, such as dilution number 5 or 6 in below. Patients with lesser sensitivity may be started with 0.05 to 0.1 mL of the next higher concentration. The amount of Allergenic Extract is increased at each injection by no more than 50% of the previous amount, and the next increment is governed by the response to the last injection. Large local reactions which persist for longer than 24 hours are generally considered an indication for repeating the previous dose or reducing the dose at the next administration. Any evidence of systemic reaction is an indication for a reduction of 75% in the subsequent dose. The upper limits of dosage have not been established; however, doses larger than 0.2 mL of an extract in 50% glycerin may cause discomfort upon injection. The dosage of Allergenic Extract does not vary significantly with the allergic disease under treatment.

To prepare dilutions starting from a concentrate such as 1:10 W/V, 1:20 W/V, OR 20,000 PNU/mL, proceed as in Table 1 below. (Note: Add 0.5 mL of concentrate to 4.5 mL of sterile diluent and make additional dilutions in the same manner.)

TABLE 1

Ten-Fold Dilution Series [There is no direct potency correlation across the table between PNUs and W/V.]
Dilution | Extract | Diluent | W/V | W/V | PNU/mL
0 | Concentrate |  | 1:10 | 1:20 | 20,000
1 | 0.5 mL in dilution concentrate | 4.5 mL | 1:100 | 1:200 | 2,000
2 | 0.5 mL in dilution 1 | 4.5 mL | 1:1,000 | 1:2,000 | 200
3 | 0.5 mL in dilution 2 | 4.5 mL | 1:10,000 | 1:20,000 | 20
4 | 0.5 mL in dilution 3 | 4.5 mL | 1:100,000 | 1:200,000 | 2
5 | 0.5 mL in dilution 4 | 4.5 mL | 1:1,000,000 | 1:2,000,000 | 0.2
6 | 0.5 mL in dilution 5 | 4.5 mL | 1:10,000,000 | 1:20,000,000 | 0.0

HOW SUPPLIED

Stock concentrate extracts containing up to 40,000 PNU/mL, or 1:10 W/V or other dilutions as requested by the physician are supplied in 5, 10, 30 and 50 mL in aqueous or 50% glycerin buffered saline. House dust extract is supplied in a 1:1 W/V concentrate, or a maximum of 10,000 PNU/mL. Extracts are also supplied in dropper vials for scratch or prick testing.

STORAGE AND HANDLING

Allergenic Extracts should be stored at 2‑8°C and kept at this temperature range during office use. Refer to vial labels for expiration dates. Diluted extracts are inherently less stable than concentrates. Dilutions of glycerinated extracts which result in glycerin below 50% are also less stable. The more dilute extracts in aqueous diluents should be replenished daily. Potency of a particular dilution can be checked by skin test in comparison to a fresh dilution of the extract on an individual known to be allergic to the specific antigen.

REFERENCES

1. Lichtenstein LM, Ishizaka K, Norman PS, et al. IgE antibody measurements in ragweed hayfever: relationship to clinical severity and the results of immunotherapy. J Clin Invest 1973;52:474.
2. Elgefors B, Julin A, Johansson SGO. Immunoglobulin E in bronchial asthma. Acta Allergol 1974;29:327.
3. Norman PS. The clinical significance of IgE. Hosp Pract 1975;10:41‑49.
4. Bryant DA, Burns MW, Lazarus L. The correlation between skin tests, bronchial provocation tests and the serum level of IgE specific for common allergens in patients with asthma. Clin Allergy 1975;5:145.
5. Loeffler JA, Cawley LP, Moeder M. Serum IgE levels: correlation with skin test sensitivity. Ann Allergy 1973;31:331.
6. Pepys J. Skin tests in diagnosis. In Gell PGH, Coombs RRA, Lachman PJ, eds. Clinical aspects of Immunology. Oxford: Blackwell Scientific Publications, 1975.
7. Burrows B, et al. Respiratory disorders and allergy skin test reactions. Ann Allergy 1976;84:134.
8. Implementation of Efficacy Review, Allergenic Extracts. Federal Register 1985;50:3082‑3288
9. Levy DA, Lichenstein LM, Goldstein EO, Ishizaka K. Immunologic and cellular changes accompanying the therapy of pollen allergy. J Clin Invest 1973;50:360.
10. Gurka G, Rocklin R. Immunologic responses during allergen-specific immunotherapy for respiratory allergy. Ann Allergy 1988;61:239-43.
11. Zeiss CR Jr. Patient evaluation. In: Allergy and Clinical Immunology, Locky RF, ed. Garden City, N.Y.: Medical Examination Publishing 1976:616.
12. Frankland AW, Augustin R. Prophylaxis of summer hay‑fever and asthma: a controlled trial comparing crude grass‑pollen extracts with the isolated main protein component. Lancet 1954;1:1055.
13. Frankland AW, Augustin R. Grass pollen antigens effective in treatment. Clin Sci 1962;23:95.
14. Rohr AS, Marshall NA, Saxon A: Successful immunotherapy for Triatoma protracta‑induced anaphylaxis. J Allergy Clin Immunol 1984;73:369‑75.
15. Executive Committee, American Academy of Allergy and Immunology. The waiting period after allergen skin testing and immunotherapy (Position statement). J Allergy Clin Immunol 1990;85:526‑7.
16. Greenberg MA, Kaufman CR, Gonzalez GE, Rosenblatt CD, Smith LJ, Summers RJ. Late and immediate systemic‑allergic reactions to inhalant allergen immunotherapy. J Allergy Clin Immunol 1986;77:865‑70.
17. Ouellette JJ. Emergency management of the allergic reactions. Modern Medicine 1975;99.
18. Anderson JA, et al. Personnel and equipment to treat systemic reactions caused by immunotherapy with allergenic extracts. J Allergy Clin Immunol 1986;77:271‑3.
19. Sadan N, Rhyne MB, Mellits ED, et al. Immunotherapy of pollenosis in children: investigation of the immunologic basis of clinical improvement. N Eng J Med 1969;280:623.
20. Johnstone DE. Value of hyposensitization therapy for perennial bronchial asthma in children. Pediatrics 1961;27:39.
21. VanAsperin PP, Kemp AS, Mellis CM. Skin test reactivity and clinical allergen sensitivity in infancy. J Allergy Clin Immunol 1984;73:381‑6.
22. Committee on Safety of Medicine. Desensitizing vaccines. Br Med J 1986;293:948.
23. Lockey RF, Benedict LM, Turkeltaub PC, Bukantz SC. Fatalities from immunotherapy (IT) and skin testing (ST). J Allergy Clin Immunol 1987;79:660‑77.
24. Norman PS, Van Metre TE Jr. The safety of allergenic immunotherapy. J Allergy Clin Immunol 1990;85:522‑5.